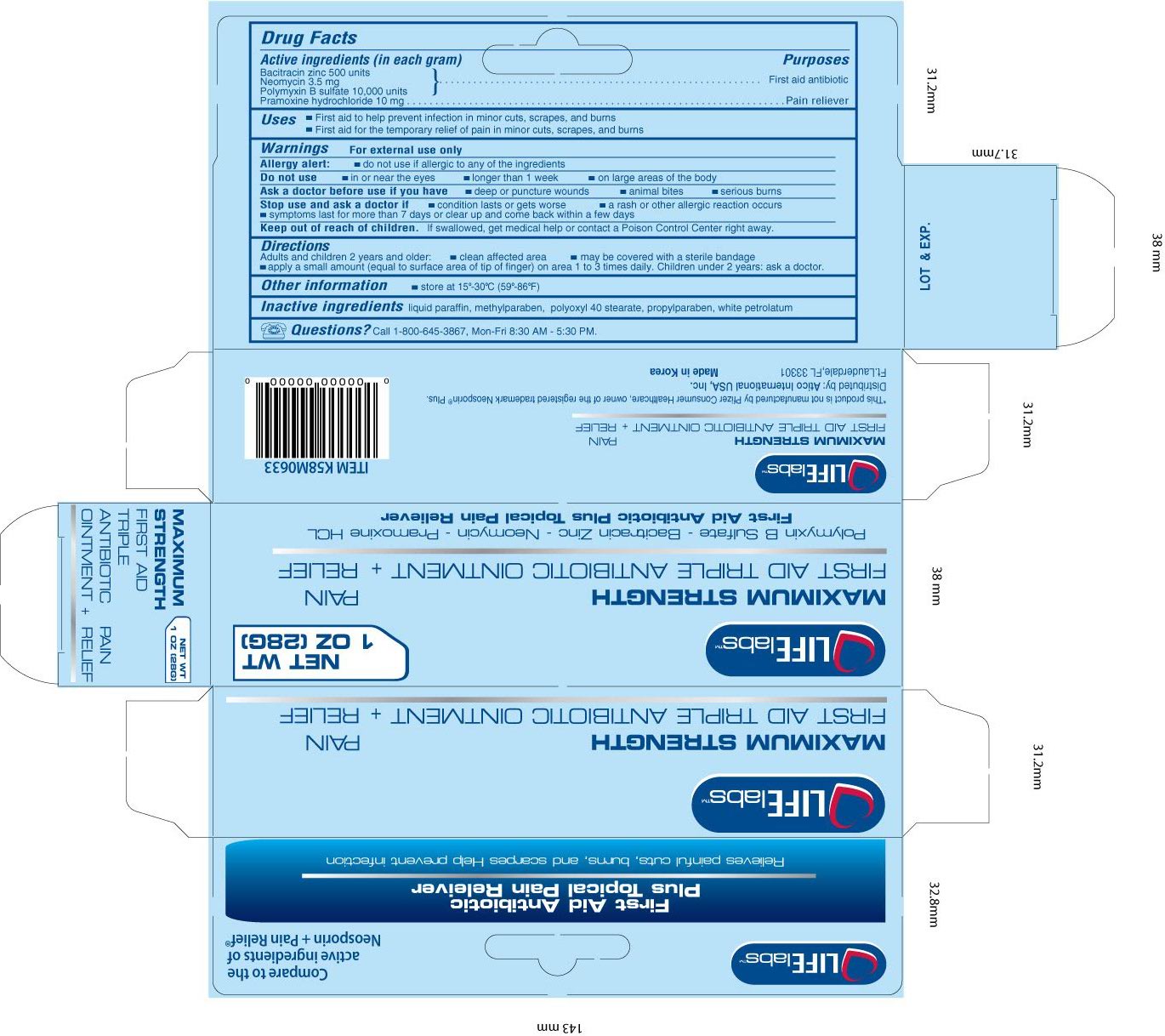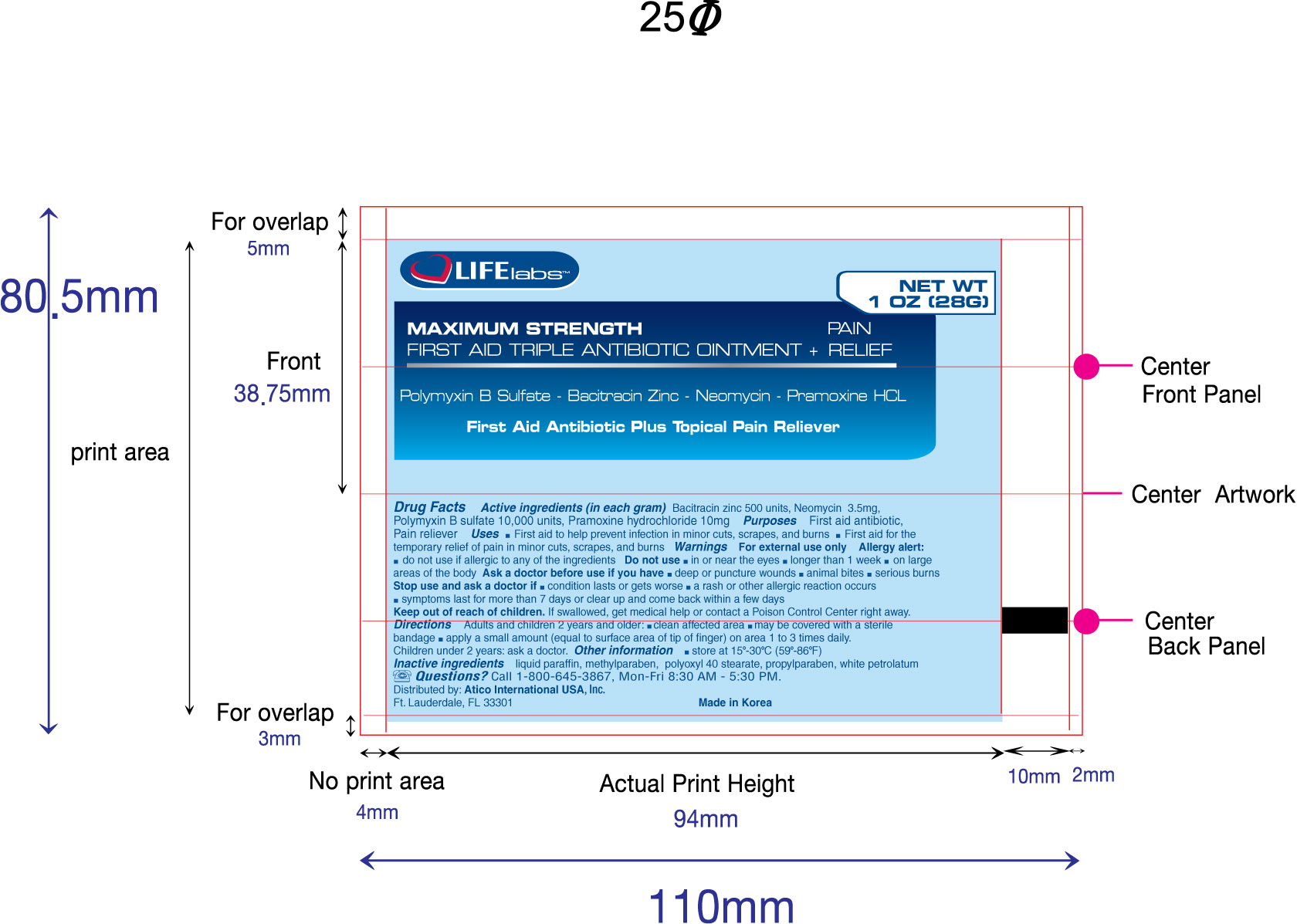 DRUG LABEL: First Aid Triple Antibiotic and Pain Relief
NDC: 51852-100 | Form: OINTMENT
Manufacturer: LIFElabs, a Division of Atico International USA, INC.
Category: otc | Type: HUMAN OTC DRUG LABEL
Date: 20100823

ACTIVE INGREDIENTS: Bacitracin Zinc 500 [USP'U]/1 g; Neomycin Sulfate 3.5 mg/1 g; Polymyxin B Sulfate 10000 [USP'U]/1 g; Pramoxine Hydrochloride 10 mg/1 g
INACTIVE INGREDIENTS: Mineral Oil; Methylparaben; Polyoxyl 40 Stearate; Propylparaben; Petrolatum

LIFElabs, a Division of Atico International USA, INC.

First Aid Triple Antibiotic and Pain Relief (Maximum Strength)

Active Ingredients

Bacitracin zinc 500 units

Neomycin 3.5 mg

Polymyxin B sulfate 10,000 units

Pramoxine hydrochloride 10 mg

Purposes

- First aid antibiotic
- Pain reliever

Warnings

For external use only

Allergy alert:

- do not use if allergic to any of the ingredients

Do not use

- in or near eyes
- longer than 1 week
- on large areas of the body

Ask a doctor before use if you have

- deep or puncture wounds
- animal bites
- serious burns

Stop use and ask a doctor if

- condition lasts or gets worse
- a rash or other allergic reaction occurs
- symptoms last for more than 7 days or clear up and come back within a few days

Keep out of reach of children.

If swallowed, get medical help or contact a Poison Control Center right away.

Directions

Adults and children 2 years and older:

- clean affected area
- may be covered with a sterile bandage
- apply a small amount (equal to surface area of tip of finger) on area 1 to 3 times daily.

Children under 2 years: ask a doctor

Other information

store at 59o - 86oF (15o - 30oC)

Inactive Ingredients

liquid paraffin, methylparaben, polyoxyl 40 stearate, propylparaben, white petrolatum

Questions?

Call 1-800-645-3867, Mon-Fri 8:30 AM - 5:30 PM.

Uses

- First aid to help prevent infection in minor cuts, scrapes, and burns
- First aid for the temporary relief of pain in minor cuts, scrapes, and burns